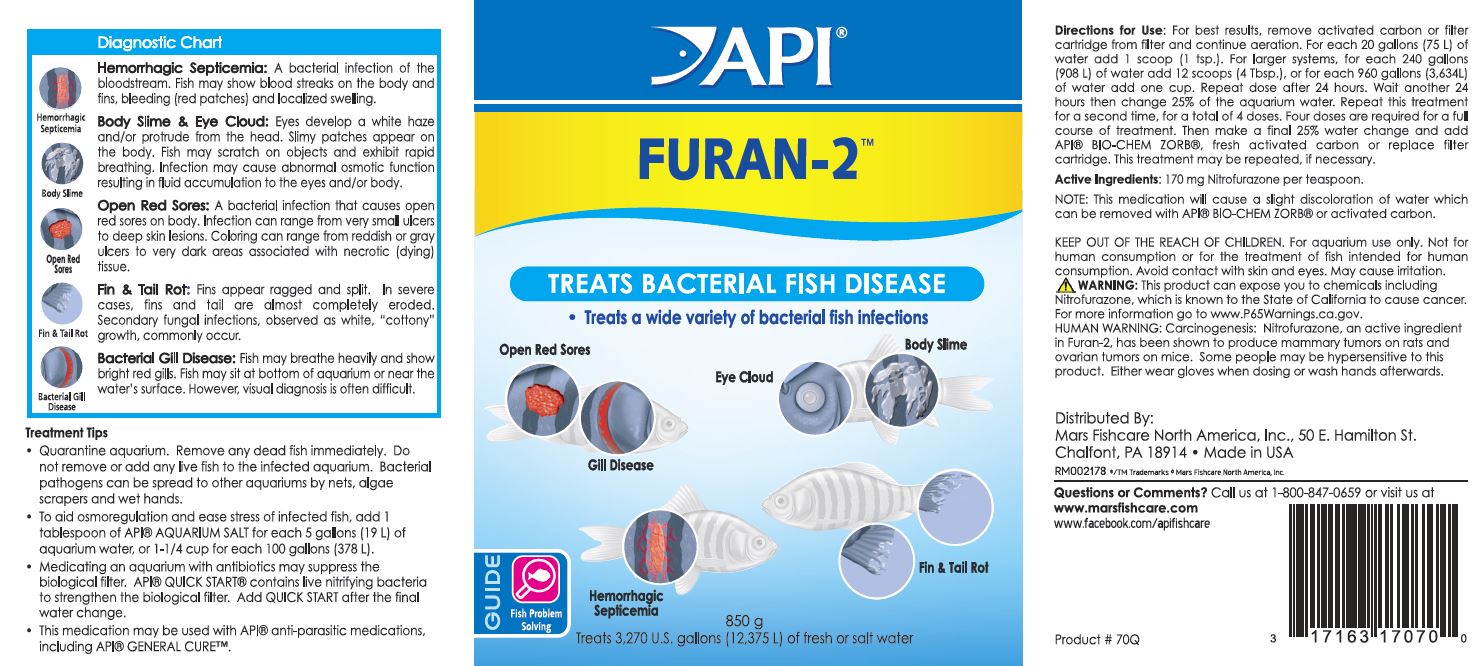 DRUG LABEL: API FURAN-2
NDC: 17163-071 | Form: POWDER
Manufacturer: MARS FISHCARE NORTH AMERICA, INC.
Category: animal | Type: OTC ANIMAL DRUG LABEL
Date: 20211229

ACTIVE INGREDIENTS: NITROFURAZONE 170 mg/5.2 g

Drug label

Active Ingredients: 170 mg Nitrofurazone per teaspoon.

DOSAGE AND ADMINISTRATION

Directions for Use:

For best results, remove activated carbon or filter cartridge from filter and continue aeration.

For each 20 gallons (75 L) of water add 1 scoop (1 tsp.).

For larger systems, for each 240 gallons (908 L) of water add 12 scoops (4 Tbsp.), or for each 960 gallons (3,634 L) of water add one cup.

Repeat dose after 24 hours.

Wait another 24 hours thenchange 25% of the aquarium water.

Repeat this treatment for a second time, for a total of 4 doses.

Four doses are required for a full course of treatment.

Then make a final 25% water change and add API BIO-CHEM ZORB, fresh activated carbon or replace filter cartridge.

This treatment may be repeated, if necessary.

NOTE: This medication will cause a slight discoloration of water which can be removed with API BIO-CHEM ZORB or activated carbon.

WARNINGS AND PRECAUTIONS

KEEP OUT OF THE REACH OF CHILDREN.

For aquarium use only.

Not for human consumption or for the treatment of fish intended for human consumption.

Avoid contact with skin and eyes.

May cause irritation.

! WARNING:

This product can expose you to chemicals including Nitrofurazone, which is known to the State of California to cause cancer.

For more information go to www.P65Warnings.ca.gov.

HUMAN WARNING:

Carcinogenesis: Nitrofurazone, an active ingredient in Furan-2, has been shown to produce mammary tumors on rats and ovarian tumors on mice.

Some people may be hypersensitive to this products.

Either wear gloves when dosing or wash hands afterwards.

INDICATIONS AND USAGE

Diagnostic Chart

Hemorrhagic Septicemia:

A bacterial infection of the bloodstream. Fish may show blood streaks on the body and fins, bleeding (red patches) and localized swelling.

Body Slime and Eye Cloud:

Eyes develop a white haze and/or protrude from the head. Slimy patches appear on the body. Fish may scratch on objects and exhibit rapid breathing. Infection may cause abnormal osmotic function resulting in fluid accumulation to the eyes and/or body.

Open Red Sores:

A bacterial infection that causes open red sores on body. Infection can range from very small ulcers to deep skin lesions. Coloring can range from reddish or gray ulcers to very dark areas associated with necrotic (dying) tissue.

Fin and Tail Rot:

Fins appear ragged and split. In severe cases, fins and tail are almost completely eroded.Secondary fungal infections, observed as white, "cottony" growth, commonly occur.

Bacterial Gill Disease:

Fish may breathe heavily and show bright red gills. Fish may sit at bottom of aquarium or near the water's surface. However, visual diagnosis is often difficult.

Treatment Tips

Quarantine aquarium. Remove any dead fish immediately. Do not remove or add any live fish to the infected aquarium. Bacterial pathogens can be spread to other aquariums by nets, algae scrapers and wet hands.

To aid osmoreregulation and ease stress of infected fish, add 1 tablespoon of API AQUARIUM SALT for each 5 gallons (19 L) of aquarium water, or 1-1/4 cup for each 100 gallons (378 L).

Medicating an aquarium with antibiotics may suppress the biological filter. API QUICK START contains live nitrifying bacteria to strengthen the biological filter. Add QUICK START after the final water change.

This medication may be used with API anti-parasitic medications, including API GENERAL CURE.

PACKAGE LABEL

API

FURAN-2

TREATS BACTERIAL FISH DISEASE

Treats a wide variety of bacterial fish infections

Open Red Sores

Gill Disease

Eye Cloud

Body Slime

Hemorrhagic Septicemia

Fin and Tail Rot

GUIDE

Fish Problem

Solving

850 g

Treats 3,270 U.S. gallons (12,375 L) of fresh or salt water